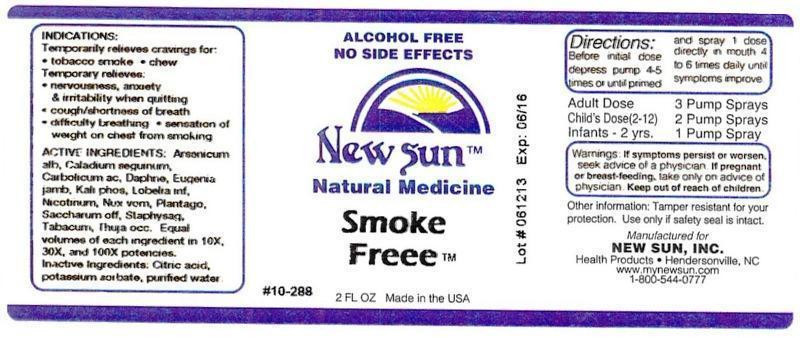 DRUG LABEL: Smoke Freee
NDC: 66579-0075 | Form: LIQUID
Manufacturer: New Sun Inc.
Category: homeopathic | Type: HUMAN OTC DRUG LABEL
Date: 20141020

ACTIVE INGREDIENTS: ARSENIC TRIOXIDE 10 [hp_X]/59 mL; DIEFFENBACHIA SEGUINE 10 [hp_X]/59 mL; PHENOL 10 [hp_X]/59 mL; DAPHNE ODORA BARK 10 [hp_X]/59 mL; SYZYGIUM JAMBOS SEED 10 [hp_X]/59 mL; POTASSIUM PHOSPHATE, DIBASIC 10 [hp_X]/59 mL; LOBELIA INFLATA 10 [hp_X]/59 mL; NICOTINE 10 [hp_X]/59 mL; STRYCHNOS NUX-VOMICA SEED 10 [hp_X]/59 mL; PLANTAGO MAJOR 10 [hp_X]/59 mL; SUCROSE 10 [hp_X]/59 mL; DELPHINIUM STAPHISAGRIA SEED 10 [hp_X]/59 mL; TOBACCO LEAF 10 [hp_X]/59 mL; THUJA OCCIDENTALIS LEAFY TWIG 10 [hp_X]/59 mL
INACTIVE INGREDIENTS: CITRIC ACID MONOHYDRATE; POTASSIUM SORBATE; WATER

Smoke Freee

DOSAGE AND ADMINISTRATION

Directions: Before initial dose depress pump 4-5 times or until primed and spray 1 dose directly in mouth 4 to 6 times daily until symptoms improve.

Adult Dose: 3 Pump Sprays

Child's Dose (2-12): 2 Pump Sprays

Infants - 2 yrs: 1 Pump Spray

WARNINGS

Warnings: If symptoms persist or worsen, seek advice of a physician. If pregnant or breast-feeding, take only on advice of physician.

Keep out of reach of children.

Other information: Tamper resistant for your protection. Use only if safety seal is intact.

PURPOSE

Indications: Temporarily relieves cravings for: • tobacco smoke • chew

Temporary relieves: • nervousness, anxiety & irritability when quitting • cough/shortness of breath • difficulty breathing • sensation of weight on chest from smoking

ACTIVE INGREDIENT

Active Ingredients: Arsenicum album, Caladium seguinum, Carbolicum acidum, Daphne indica, Eugenia jambosa, Kali phosphoricum, Lobelia inflata, Nicotinum, Nux vomica, Plantago major, Saccharum officinale, Staphysagria, Tabacum, Thuja occidentalis. Equal volumes of each ingredient in 10X, 30X, and 100X potencies.

Inactive Ingredient: Citric acid, potassium sorbate, purified water.

Indications: Temporarily relieves cravings for:

- tobacco smoke
- chew

Temporary relieves:

- nervousness, anxiety & irritability when quitting
- cough/shortness of breath
- difficulty breathing
- sensation of weight on chest from smoking